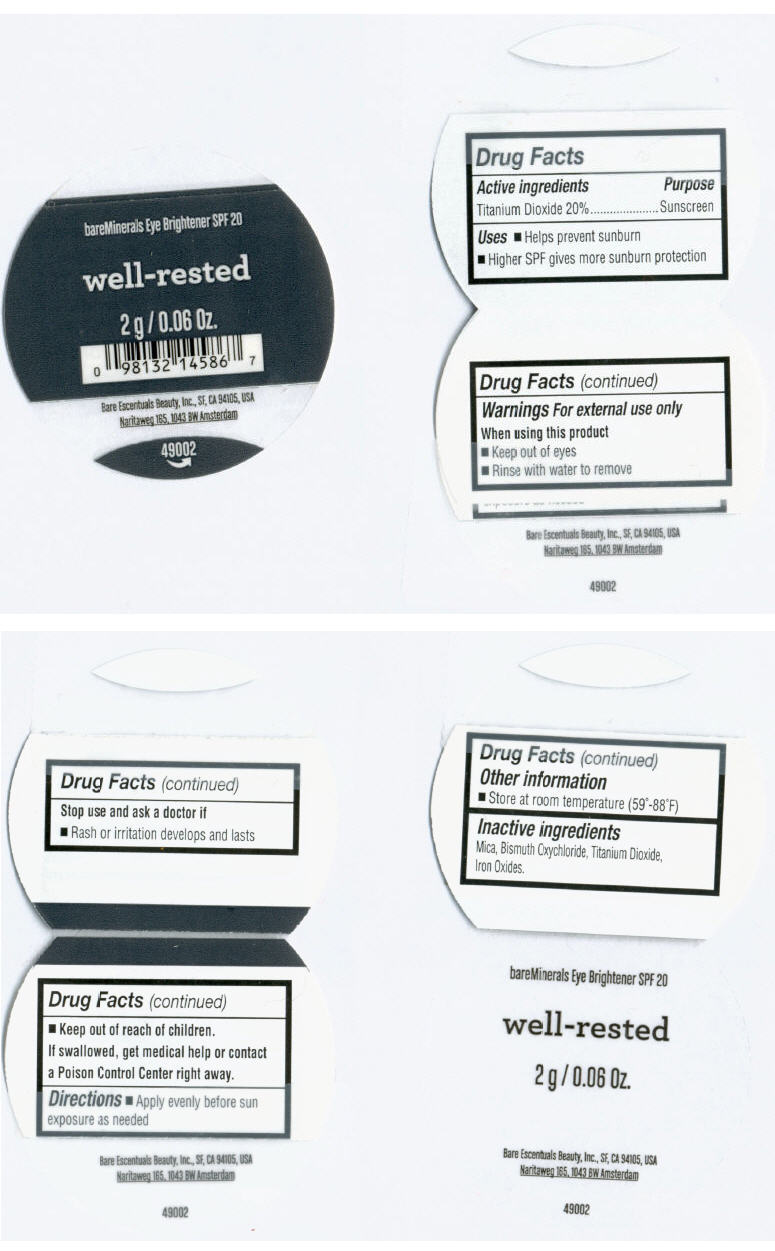 DRUG LABEL: bareMinerals
NDC: 98132-162 | Form: POWDER
Manufacturer: Bare Escentuals Beauty Inc.
Category: otc | Type: HUMAN OTC DRUG LABEL
Date: 20110726

ACTIVE INGREDIENTS: Titanium Dioxide 20 g/100 g
INACTIVE INGREDIENTS: Mica; Bismuth Oxychloride; Ferric Oxide Red

Well-Rested

Drug Facts

Active ingredients

Titanium Dioxide 20%

Purpose

Sunscreen

Uses

- Helps prevent sunburn.
- Higher SPF gives more sunburn protection.

Warnings

For external use only

When using this product

- Keep out of Eyes ;
- Rinse with water to remove

Stop use and ask a doctor if

- Rash or irritation developes and lasts.

- Keep out of reach of children.

If swallowed, get medical help or contact a Poison Control Center right away.

Directions

- Apply evenly before sun exposure as needed.

Other information

- Store at room temperature (59° to 86° F)

Inactive ingredients

Mica, Bismuth Oxychloride, Titanium Dioxide, Iron Oxides.

Distr. By Bare Escentuals Beauty Inc., San Francisco CA 94104 USA

PRINCIPAL DISPLAY PANEL - 2 g Jar Label

bareMinerals Eye Brightener SPF 20

well-rested

2 g / 0.06 Oz.